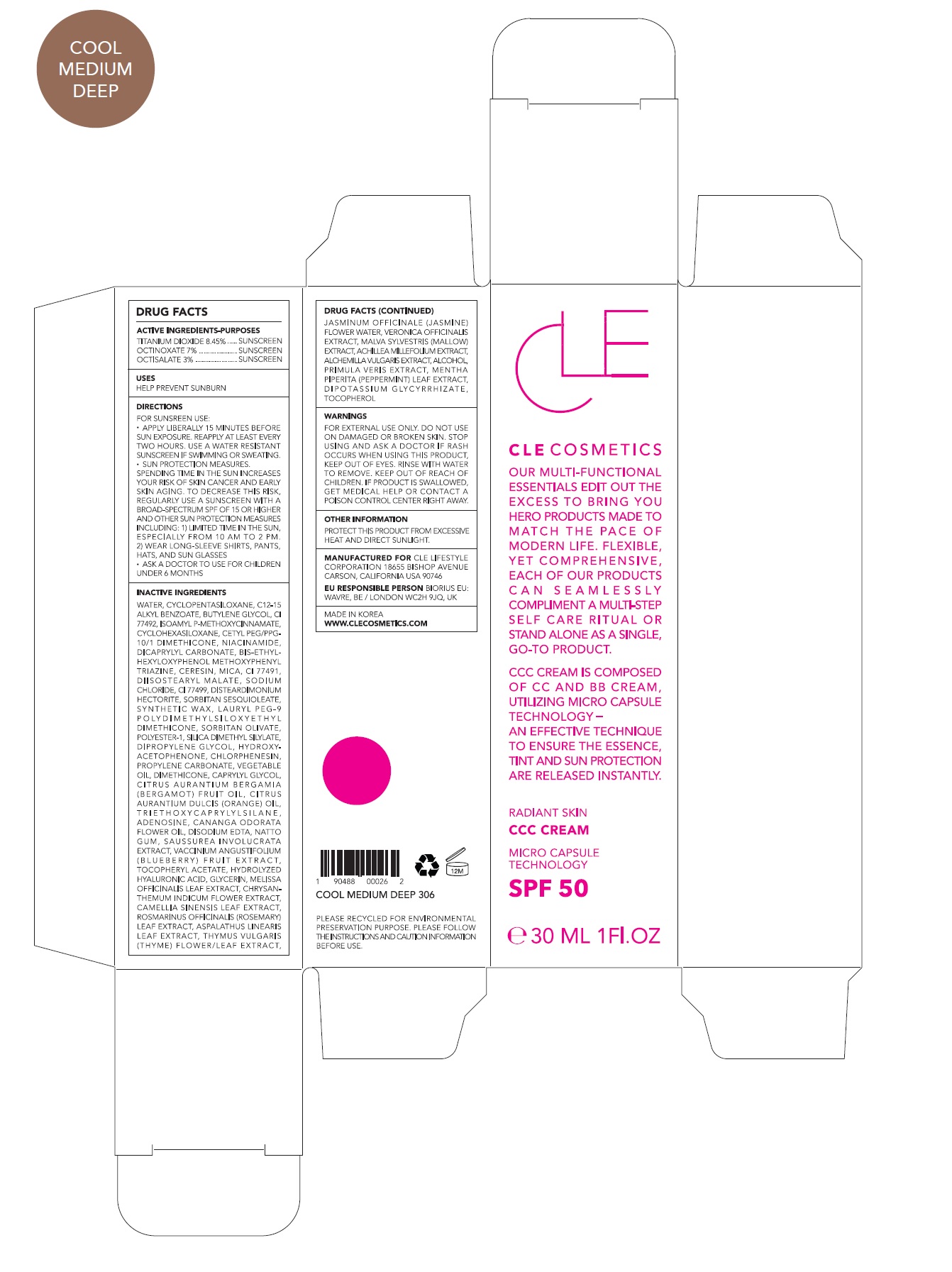 DRUG LABEL: CLE CCC Cool Medium Deep
NDC: 69231-031 | Form: CREAM
Manufacturer: KW ABSC, INC.
Category: otc | Type: HUMAN OTC DRUG LABEL
Date: 20241219

ACTIVE INGREDIENTS: OCTINOXATE 2.1 mg/30 mL; OCTISALATE 0.9 mg/30 mL; TITANIUM DIOXIDE 2.535 mg/30 mL
INACTIVE INGREDIENTS: WATER; CYCLOMETHICONE 5; ALKYL (C12-15) BENZOATE; CYCLOMETHICONE 6; FERRIC OXIDE YELLOW; BUTYLENE GLYCOL; AMILOXATE; CETYL PEG/PPG-10/1 DIMETHICONE (HLB 2); NIACINAMIDE; DICAPRYLYL CARBONATE; MICA; BEMOTRIZINOL; CERESIN; FERRIC OXIDE RED; DIISOSTEARYL MALATE; SODIUM CHLORIDE; FERROSOFERRIC OXIDE; POLYESTER-10; SILICA DIMETHYL SILYLATE; DISTEARDIMONIUM HECTORITE; SORBITAN SESQUIOLEATE; SYNTHETIC WAX (1200 MW); LAURYL PEG-9 POLYDIMETHYLSILOXYETHYL DIMETHICONE; SORBITAN OLIVATE; CORN OIL; CHLORPHENESIN; DIPROPYLENE GLYCOL; BERGAMOT OIL; ORANGE OIL; PROPYLENE CARBONATE; 1,2-HEXANEDIOL; HYDROXYACETOPHENONE; DIMETHICONE; PHENYL TRIMETHICONE; CANANGA OIL; DIMETHICONE CROSSPOLYMER (450000 MPA.S AT 12% IN CYCLOPENTASILOXANE); ADENOSINE; EDETATE DISODIUM ANHYDROUS

69231-031_CLE CCC Cool Medium Deep

ACTIVE INGREDIENT

Titanium Dioxide 8.45%

Ethylhexyl Methoxycinnamate 7.00%

Ethylhexyl Salicylate 3.00%

PURPOSE

Sunscreen

INDICATIONS AND USAGE

Helps prevent sunburn

DOSAGE AND ADMINISTRATION

Apply liberally 15 minutes before sun exposure. Reapply at least every two hours

Sun protection measures. Spending time in the sun increases your risk of skin cancer and early skin aging. To decrease this risk, regularly use a sunscreen with a broad spectrum SPF of 15 of higher and other sun protection measures including: 1) Limited time in the sun, especially from 10 am to 2 pm. 2) Wear long-sleeve shirts, pants, hats, and sunglasses
Ask a doctor to use for children under 6 months

WARNINGS

For external use only.
Do not use on damaged or broken skin.
When using this product, keep out of eyes. Rinse with water to remove.
Stop using and ask a doctor if rash occurs.

KEEP OUT OF REACH OF CHILDREN

Keep out of reach of the children. If product is swallowed, get medical help or contact a poison control center right away.

INACTIVE INGREDIENT

Water, Cyclopentasiloxane, C12-15 Alkyl Benzoate, Butylene Glycol, CI 77492, Isoamyl p-Methoxycinnamate, Cyclohexasiloxane, Cetyl PEG/PPG-10/1 Dimethicone, Niacinamide, Dicaprylyl Carbonate, Bis-Ethylhexyloxyphenol Methoxyphenyl Triazine, Ceresin, Mica, CI 77491, Diisostearyl Malate, Sodium Chloride, CI 77499, Disteardimonium Hectorite, Sorbitan Sesquioleate, Synthetic Wax, Lauryl PEG-9 Polydimethylsiloxyethyl Dimethicone, Sorbitan Olivate, Polyester-1, Silica Dimethyl Silylate, Dipropylene Glycol, Hydroxyacetophenone, Chlorphenesin, Propylene Carbonate, Vegetable Oil, Dimethicone, Caprylyl Glycol, Citrus Aurantium Bergamia (Bergamot) Fruit Oil, Citrus Aurantium Dulcis (Orange) Oil, Triethoxycaprylylsilane, Adenosine, Cananga Odorata Flower Oil, Disodium EDTA, Natto Gum, Saussurea Involucrata Extract, Vaccinium Angustifolium (Blueberry) Fruit Extract, Tocopheryl Acetate, Hydrolyzed Hyaluronic Acid, Glycerin, Melissa Officinalis Leaf Extract, Chrysanthemum Indicum Flower Extract, Camellia Sinensis Leaf Extract, Rosmarinus Officinalis (Rosemary) Leaf Extract, Aspalathus Linearis Leaf Extract, Thymus Vulgaris (Thyme) Flower/Leaf Extract, Jasminum Officinale (Jasmine) Flower Water, Veronica Officinalis Extract, Malva Sylvestris (Mallow) Extract, Achillea Millefolium Extract, Alchemilla Vulgaris Extract, Alcohol, Primula Veris Extract, Mentha Piperita (Peppermint) Leaf Extract, Dipotassium Glycyrrhizate, Tocopherol